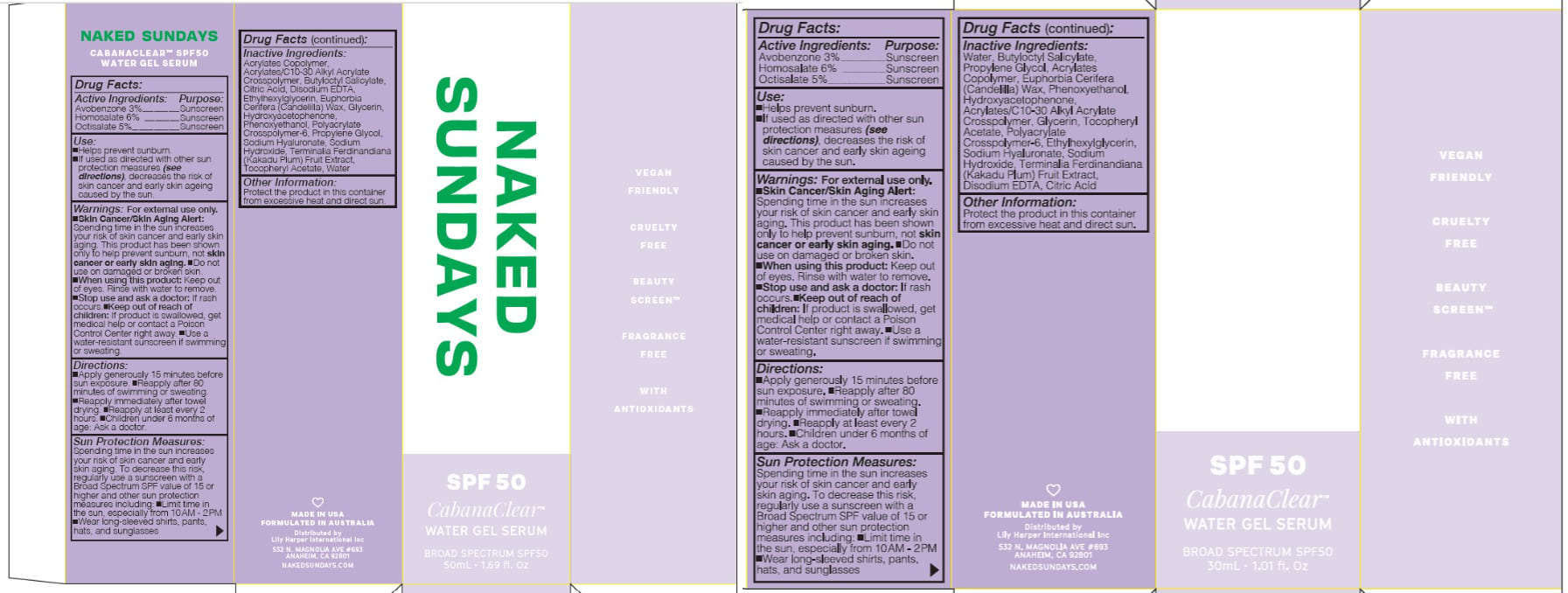 DRUG LABEL: BROAD SPECTRUM SPF50

NDC: 81104-801 | Form: GEL
Manufacturer: NAKED SUNDAYS PTY LTD
Category: otc | Type: HUMAN OTC DRUG LABEL
Date: 20250401

ACTIVE INGREDIENTS: AVOBENZONE 3 g/100 mL; HOMOSALATE 10 g/100 mL; OCTISALATE 5 g/100 mL
INACTIVE INGREDIENTS: CITRIC ACID MONOHYDRATE; HYALURONATE SODIUM; EDETATE DISODIUM ANHYDROUS; ALPHA-TOCOPHEROL ACETATE; POLYACRYLATE-1 CROSSPOLYMER; GLYCERIN; ETHYLHEXYLGLYCERIN; SODIUM HYDROXIDE; KAKADU PLUM; WATER; BUTYLOCTYL SALICYLATE; PROPYLENE GLYCOL; ACRYLATES CROSSPOLYMER-4; PHENOXYETHANOL; HYDROXYACETOPHENONE

NAKED SUNDAYS CABANA CLEAR WATER GEL SERUM 30mL

ACTIVE INGREDIENTS

Avobenzone 3%

Homosalate 10%

Octilsalate 5%

Purpose

Sunscreen

USES

Helps prevent sunburn.
If used as directed with other sun
protection measures (see
directions), decreases the risk of
skin cancer and early skin ageing
caused by the sun.

WARNINGS

Warnings: For external use only.
Skin Cancer/Skin Aging Alert:
Spending time in the sun increases
your risk of skin cancer and early skin
aging. This product has been shown
only to help prevent sunburn, not skin
cancer or early skin aging. Do not
use on damaged or broken skin.
When using this product: Keep out
of eyes. Rinse with water to remove.
Stop use and ask a doctor: If rash
occurs. Keep out of reach of
children: If product is swallowed, get
medical help or contact a Poison
Control Center right away. Use a
water-resistant sunscreen if swimming
or sweating.

Keep out of reach of children. If product is swallowed, get medical help or contact a Poison Control Center right away.

DIRECTIONS

- SPRAY 7 TIMES WITH MOUTH AND LIPS CLOSED 8-10" AWAY FROM FACE 15 MINUTES BEFORE SUN EXPOSURE.
- Reapply after 80 minutes of swimming or sweating.
- Reapply immediately after towel drying.
- Reapply at least every 2 hours.
- Children under 3 years of age: Ask a doctor.

SUN PROTECTION MEASURES:

Spending time in the sun increases your risk of skin cancer and early skin aging. To decrease this risk, regularly use a sunscreen with a Broad Spectrum SPF value of 15 or higher and other sun protection measures including:

- Limit time in the sun, especially from 10.00AM - 2.00PM
- Wear long-sleeved shirts, pants, hats, and sunglasses

INACTIVE INGREDIENTS

Water, Butyloctyl Salicylate,
Propylene Glycol, Acrylates
Copolymer, Euphorbia Cerifera
(Candelilla) Wax, Phenoxyethanol,
Hydroxyacetophenone,
Acrylates/C10-30 Alkyl Acrylate
Crosspolymer, Glycerin, Tocopheryl
Acetate, Polyacrylate
Crosspolymer-6, Ethylhexylglycerin,
Sodium Hyaluronate, Sodium
Hydroxide, Terminalia Ferdinandiana
(Kakadu Plum) Fruit Extract,
Disodium EDTA, Citric Acid

OTHER INFORMATION

Protect the product in this container
from excessive heat and direct sun.

USER SAFETY WARNINGS

Directions: Apply generously 15 minutes before
sun exposure. Use a water-resistant sunscreen if
swimming or sweating. Reapply immediately after
towel drying. Reapply at least every 2 hours.
Sun Protection Measures: Spending time in the
sun increases your risk of skin cancer and early skin
aging. To decrease this risk, regularly use a
sunscreen with a Broad Spectrum SPF value of 15 or
higher and other sun protection measures including:
Limit time in the sun, especially from 10AM - 2PM
Wear long-sleeved shirts, pants, hats, and
sunglasses Children under 6 months of age: Ask a
doctor.

Directions:
Apply generously 15 minutes before
sun exposure. Reapply after 80
minutes of swimming or sweating.
Reapply immediately after towel
drying. Reapply at least every 2
hours. Children under 6 months of
age: Ask a doctor.

Sun Protection Measures:
Spending time in the sun increases
your risk of skin cancer and early
skin aging. To decrease this risk,
regularly use a sunscreen with a
Broad Spectrum SPF value of 15 or
higher and other sun protection
measures including: Limit time in
the sun, especially from 10AM - 2PM
Wear long-sleeved shirts, pants,
hats, and sunglasses